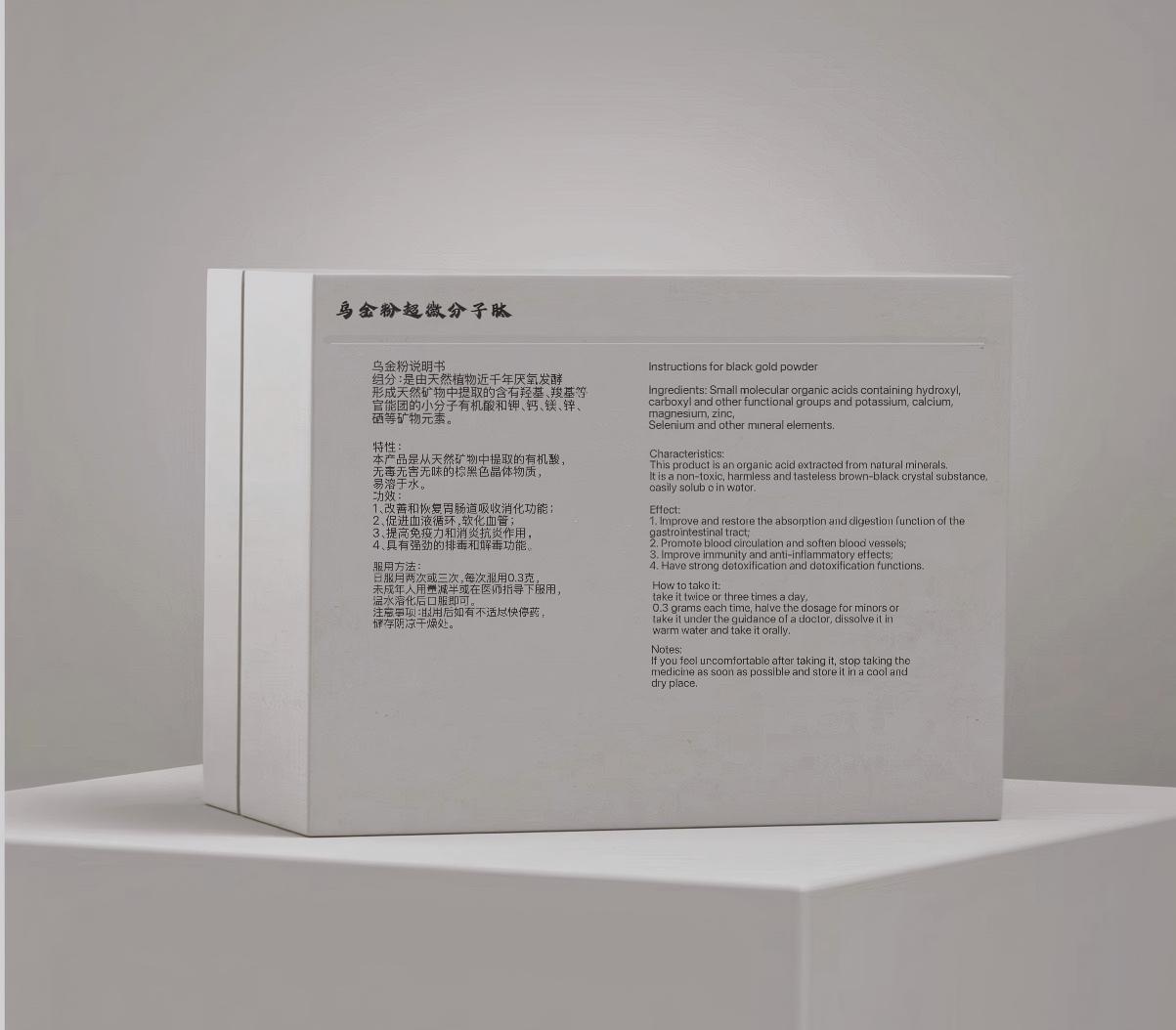 DRUG LABEL: Black gold
NDC: 87114-371 | Form: POWDER
Manufacturer: Zhongbaokang Biotechnology Co., Ltd
Category: homeopathic | Type: HUMAN OTC DRUG LABEL
Date: 20250924

ACTIVE INGREDIENTS: SELENIUM 16 mg/1 1
INACTIVE INGREDIENTS: MAGNESIUM CATION; ZIFOGAPTIDE; FERROUS CATION; CALCIUM CATION

INACTIVE INGREDIENT

Yellow Fulvic Acid Peptide,Ferrous Ion,Active Calcium Ion,Magnesium Ion

ACTIVE INGREDIENT

Selenium

PURPOSE

Improve and restore gastrointestinal absorption and digestive function.

WARNINGS

Keep it out of reach of children.

Keep it out of reach of children.

INDICATIONS AND USAGE

Take 0.3 grams twice or three times a day.

DOSAGE AND ADMINISTRATION

Take 0.3 grams twice or three times a day.